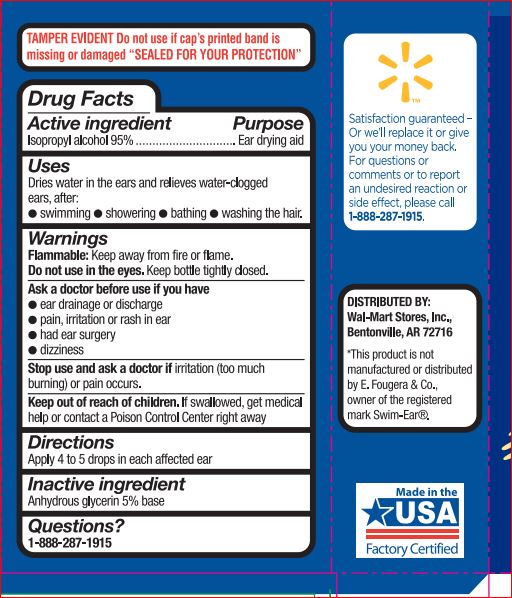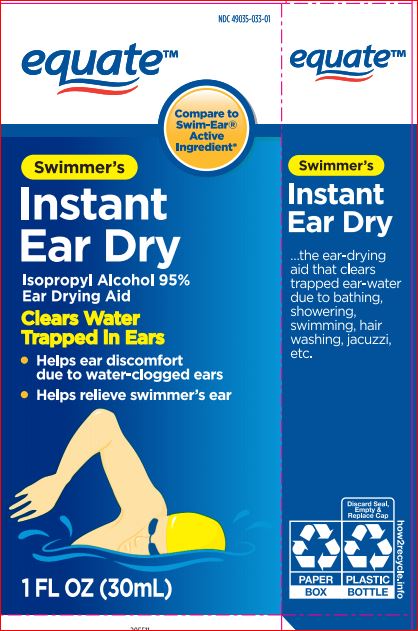 DRUG LABEL: Instant Ear Dry

NDC: 49035-033 | Form: SOLUTION/ DROPS
Manufacturer: WalMart
Category: otc | Type: HUMAN OTC DRUG LABEL
Date: 20180102

ACTIVE INGREDIENTS: ISOPROPYL ALCOHOL 0.95 g/100 mL
INACTIVE INGREDIENTS: GLYCERIN

Active ingredient Purpose

ISOPROPYL ALCOHOL 95.0%

Uses
Dries water in the ears and relieves water-clogged ears, thereby relieving discomfort, the sensation of fullness or hearing impairment

Warnings

Flammable. Keep away from fire or flame

Do not use • in the eyes

Ask doctor before use if you have • ear drainage or discharge • ear pain • irritation or rash in ear • dizziness • recently had ear surgery

Stop use and ask a doctor if irritation (too much burning) or pain occurs.

Keep out of reach of the children
If product is swallowed, get medical help or contact a Poison Control Center right away
In case of accidental ingestion, seek professional or contact a Poison Control Center immediately.

Direction

Apply 4-5 drops in each affected ear

Inactive ingredient

ISOPROPYL ALCOHOL, GLYCERIN